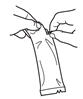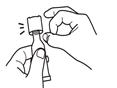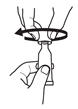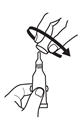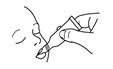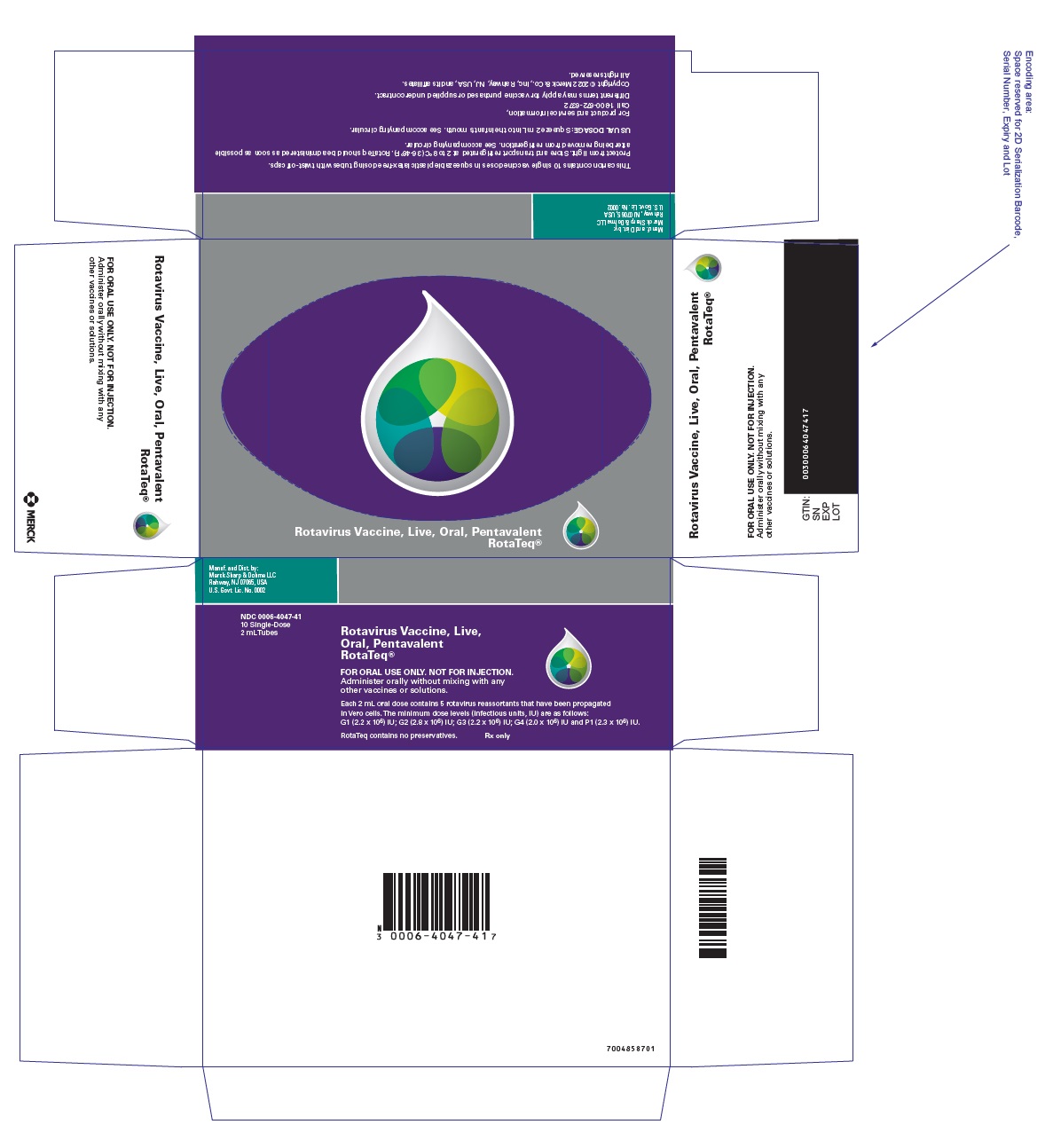 DRUG LABEL: RotaTeq
NDC: 0006-4047 | Form: SOLUTION
Manufacturer: Merck Sharp & Dohme LLC
Category: other | Type: VACCINE LABEL
Date: 20241101

ACTIVE INGREDIENTS: HUMAN ROTAVIRUS A TYPE G1P7(5) STRAIN WI79 LIVE ANTIGEN 2200000 [iU]/2 mL; HUMAN ROTAVIRUS A TYPE G2P7(5) STRAIN SC2 LIVE ANTIGEN 2800000 [iU]/2 mL; HUMAN ROTAVIRUS A TYPE G3P7(5) STRAIN WI78 LIVE ANTIGEN 2200000 [iU]/2 mL; HUMAN ROTAVIRUS A TYPE G4P7(5) STRAIN BRB LIVE ANTIGEN 2000000 [iU]/2 mL; HUMAN ROTAVIRUS A TYPE G6P1A(8) STRAIN WI79 LIVE ANTIGEN 2300000 [iU]/2 mL
INACTIVE INGREDIENTS: ALBUMIN BOVINE; POLYSORBATE 80; SODIUM HYDROXIDE; SODIUM PHOSPHATE, MONOBASIC, MONOHYDRATE; SUCROSE; SODIUM CITRATE, UNSPECIFIED FORM

HIGHLIGHTS OF PRESCRIBING INFORMATION

These highlights do not include all the information needed to use RotaTeq safely and effectively. See full prescribing information for RotaTeq.
RotaTeq® (Rotavirus Vaccine, Live, Oral, Pentavalent) Oral Solution
Initial U.S. Approval: 2006

1 INDICATIONS AND USAGE

RotaTeq is a vaccine indicated for the prevention of rotavirus gastroenteritis caused by types G1, G2, G3, G4, and G9. (1)

RotaTeq is approved for use in infants 6 weeks to 32 weeks of age. (1)

2 DOSAGE AND ADMINISTRATION

- FOR ORAL USE ONLY. NOT FOR INJECTION. (2)
- The vaccination series consists of three ready-to-use liquid doses of RotaTeq administered orally starting at 6 to 12 weeks of age, with the subsequent doses administered at 4- to 10-week intervals. The third dose should not be given after 32 weeks of age. (2)

3 DOSAGE FORMS AND STRENGTHS

2 mL solution for oral administration of 5 live human-bovine reassortant rotaviruses which contains a minimum of 2.0 – 2.8 x 10^6 infectious units (IU) per reassortant dose, depending on the reassortant, and not greater than 116 x 10^6 IU per aggregate dose. (3)

4 CONTRAINDICATIONS

- A demonstrated history of hypersensitivity to the vaccine or any component of the vaccine. (4.1)
- History of Severe Combined Immunodeficiency Disease (SCID). (4.2, 6.2)
- History of intussusception. (4.3)

5 WARNINGS AND PRECAUTIONS

- No safety or efficacy data are available from clinical trials regarding the administration of RotaTeq to infants who are potentially immunocompromised (e.g., HIV/AIDS). (5.2)
- In a post-marketing study, cases of intussusception were observed in temporal association within 21 days following the first dose of RotaTeq, with a clustering of cases in the first 7 days. (5.3, 6.2)
- No safety or efficacy data are available for the administration of RotaTeq to infants with a history of gastrointestinal disorders (e.g., active acute gastrointestinal illness, chronic diarrhea, failure to thrive, history of congenital abdominal disorders, and abdominal surgery). (5.4)
- Vaccine virus transmission from vaccine recipient to non-vaccinated contacts has been reported. Caution is advised when considering whether to administer RotaTeq to individuals with immunodeficient contacts. (5.5)

6 ADVERSE REACTIONS

Most common adverse events included diarrhea, vomiting, irritability, otitis media, nasopharyngitis, and bronchospasm. (6.1)

To report SUSPECTED ADVERSE REACTIONS, contact Merck Sharp & Dohme LLC at 1-877-888-4231 or VAERS at 1-800-822-7967 or www.vaers.hhs.gov .{4}

8 USE IN SPECIFIC POPULATIONS

Pediatric Use: Safety and efficacy have not been established in infants less than 6 weeks of age or greater than 32 weeks of age. Data are available from clinical studies to support the use of RotaTeq in:

- Pre-term infants according to their age in weeks since birth
- Infants with controlled gastroesophageal reflux disease. (8.4)

FULL PRESCRIBING INFORMATION

1 INDICATIONS AND USAGE

RotaTeq® is indicated for the prevention of rotavirus gastroenteritis in infants and children caused by types G1, G2, G3, G4, and G9 when administered as a 3-dose series to infants between the ages of 6 to 32 weeks. The first dose of RotaTeq should be administered between 6 and 12 weeks of age [see Dosage and Administration (2)].

2 DOSAGE AND ADMINISTRATION

FOR ORAL USE ONLY. NOT FOR INJECTION.

The vaccination series consists of three ready-to-use liquid doses of RotaTeq administered orally starting at 6 to 12 weeks of age, with the subsequent doses administered at 4- to 10-week intervals. The third dose should not be given after 32 weeks of age [see Clinical Studies (14)].

There are no restrictions on the infant's consumption of food or liquid, including breast milk, either before or after vaccination with RotaTeq.

Do not mix the RotaTeq vaccine with any other vaccines or solutions. Do not reconstitute or dilute [see Dosage and Administration (2.2)].

For storage instructions [see How Supplied/Storage and Handling (16.1)].

Each dose is supplied in a container consisting of a squeezable plastic dosing tube with a twist-off cap, allowing for direct oral administration. The dosing tube is contained in a pouch [see Dosage and Administration (2.2)].

2.1 Use with Other Vaccines

In clinical trials, RotaTeq was administered concomitantly with other licensed pediatric vaccines [see Adverse Reactions (6.1), Drug Interactions (7.1), and Clinical Studies (14)].

2.2 Instructions for Use

To administer the vaccine:

Tear open the pouch and remove the dosing tube.

Clear the fluid from the dispensing tip by holding tube vertically and tapping cap.

Open the dosing tube in 2 easy motions:

1. Puncture the dispensing tip by screwing cap clockwise
until it becomes tight.

2. Remove cap by turning it counterclockwise.

Administer dose by gently squeezing liquid into infant's mouth toward the inner cheek until dosing tube is empty. (A residual drop may remain in the tip of the tube.)

If for any reason an incomplete dose is administered (e.g., infant spits or regurgitates the vaccine), a replacement dose is not recommended, since such dosing was not studied in the clinical trials. The infant should continue to receive any remaining doses in the recommended series.

Discard the empty tube and cap in approved biological waste containers according to local regulations.

3 DOSAGE FORMS AND STRENGTHS

RotaTeq, 2 mL for oral use, is a ready-to-use solution of live reassortant rotaviruses, containing G1, G2, G3, G4 and P1A[8] which contains a minimum of 2.0 – 2.8 x 10^6 infectious units (IU) per individual reassortant dose, depending on the reassortant and not greater than 116 x 10^6 IU per aggregate dose.

Each dose is supplied in a container consisting of a squeezable plastic dosing tube with a twist-off cap, allowing for direct oral administration. The dosing tube is contained in a pouch.

4 CONTRAINDICATIONS

4.1 Hypersensitivity

A demonstrated history of hypersensitivity to any component of the vaccine.

Infants who develop symptoms suggestive of hypersensitivity after receiving a dose of RotaTeq should not receive further doses of RotaTeq.

4.2 Severe Combined Immunodeficiency Disease

Infants with Severe Combined Immunodeficiency Disease (SCID) should not receive RotaTeq. Post-marketing reports of gastroenteritis, including severe diarrhea and prolonged shedding of vaccine virus, have been reported in infants who were administered RotaTeq and later identified as having SCID [see Adverse Reactions (6.2)].

4.3 History of Intussusception

Infants with a history of intussusception should not receive RotaTeq.

5 WARNINGS AND PRECAUTIONS

5.1 Managing Allergic Reactions

Appropriate medical treatment and supervision must be available to manage possible anaphylactic reactions following administration of the vaccine.

5.2 Immunocompromised Populations

No safety or efficacy data are available from clinical trials regarding the administration of RotaTeq to infants who are potentially immunocompromised including:

- Infants with blood dyscrasias, leukemia, lymphomas of any type, or other malignant neoplasms affecting the bone marrow or lymphatic system.
- Infants on immunosuppressive therapy (including high-dose systemic corticosteroids). RotaTeq may be administered to infants who are being treated with topical corticosteroids or inhaled steroids.
- Infants with primary and acquired immunodeficiency states, including HIV/AIDS or other clinical manifestations of infection with human immunodeficiency viruses; cellular immune deficiencies; and hypogammaglobulinemic and dysgammaglobulinemic states. There are insufficient data from the clinical trials to support administration of RotaTeq to infants with indeterminate HIV status who are born to mothers with HIV/AIDS.
- Infants who have received a blood transfusion or blood products, including immunoglobulins within 42 days.

Vaccine virus transmission from vaccine recipient to non-vaccinated contacts has been reported [see Warnings and Precautions (5.5)].

5.3 Intussusception

Following administration of a previously licensed live rhesus rotavirus reassortant vaccine, an increased risk of intussusception was observed.{1}

In a post-marketing observational study in the US cases of intussusception were observed in temporal association within 21 days following the first dose of RotaTeq, with a clustering of cases in the first 7 days. [See Adverse Reactions (6.2).]

In worldwide passive post-marketing surveillance, cases of intussusception have been reported in temporal association with RotaTeq. [See Adverse Reactions (6.2).]

5.4 Gastrointestinal Illness

No safety or efficacy data are available for administration of RotaTeq to infants with a history of gastrointestinal disorders including infants with active acute gastrointestinal illness, infants with chronic diarrhea and failure to thrive, and infants with a history of congenital abdominal disorders, and abdominal surgery. Caution is advised when considering administration of RotaTeq to these infants.

5.5 Shedding and Transmission

Shedding of vaccine virus was evaluated among a subset of subjects in the Rotavirus Efficacy and Safety Trial (Study 006, also known as REST) 4 to 6 days after each dose and among all subjects who submitted a stool antigen rotavirus positive sample at any time. RotaTeq was shed in the stools of 32 of 360 [8.9%, 95% CI (6.2%, 12.3%)] vaccine recipients tested after dose 1; 0 of 249 [0.0%, 95% CI (0.0%, 1.5%)] vaccine recipients tested after dose 2; and in 1 of 385 [0.3%, 95% CI (<0.1%, 1.4%)] vaccine recipients after dose 3. In phase 3 studies, shedding was observed as early as 1 day and as late as 15 days after a dose. Transmission of vaccine virus was not evaluated in phase 3 studies.

Transmission of vaccine virus strains from vaccinees to non-vaccinated contacts has been observed post-marketing.

The potential risk of transmission of vaccine virus should be weighed against the risk of acquiring and transmitting natural rotavirus.

Caution is advised when considering whether to administer RotaTeq to individuals with immunodeficient close contacts such as:

- Individuals with malignancies or who are otherwise immunocompromised;
- Individuals with primary immunodeficiency; or
- Individuals receiving immunosuppressive therapy.

5.6 Febrile Illness

Febrile illness may be reason for delaying use of RotaTeq except when, in the opinion of the physician, withholding the vaccine entails a greater risk. Low-grade fever (<100.5°F [38.1°C]) itself and mild upper respiratory infection do not preclude vaccination with RotaTeq.

5.7 Incomplete Regimen

The clinical studies were not designed to assess the level of protection provided by only one or two doses of RotaTeq.

5.8 Limitations of Vaccine Effectiveness

RotaTeq may not protect all vaccine recipients against rotavirus.

5.9 Post-Exposure Prophylaxis

No clinical data are available for RotaTeq when administered after exposure to rotavirus.

6 ADVERSE REACTIONS

6.1 Clinical Studies Experience

71,725 infants were evaluated in 3 placebo-controlled clinical trials including 36,165 infants in the group that received RotaTeq and 35,560 infants in the group that received placebo. Parents/guardians were contacted on days 7, 14, and 42 after each dose regarding intussusception and any other serious adverse events. The racial distribution was as follows: White (69% in both groups); Hispanic-American (14% in both groups); Black (8% in both groups); Multiracial (5% in both groups); Asian (2% in both groups); Native American (RotaTeq 2%, placebo 1%); and Other (<1% in both groups). The gender distribution was 51% male and 49% female in both vaccination groups.

Because clinical trials are conducted under conditions that may not be typical of those observed in clinical practice, the adverse reaction rates presented below may not be reflective of those observed in clinical practice.

Serious Adverse Events

Serious adverse events occurred in 2.4% of recipients of RotaTeq when compared to 2.6% of placebo recipients within the 42-day period of a dose in the phase 3 clinical studies of RotaTeq. The most frequently reported serious adverse events for RotaTeq compared to placebo were:

bronchiolitis (0.6% RotaTeq vs. 0.7% Placebo),

gastroenteritis (0.2% RotaTeq vs. 0.3% Placebo),

pneumonia (0.2% RotaTeq vs. 0.2% Placebo),

fever (0.1% RotaTeq vs. 0.1% Placebo), and

urinary tract infection (0.1% RotaTeq vs. 0.1% Placebo).

Deaths

Across the clinical studies, 52 deaths were reported. There were 25 deaths in the RotaTeq recipients compared to 27 deaths in the placebo recipients. The most commonly reported cause of death was sudden infant death syndrome, which was observed in 8 recipients of RotaTeq and 9 placebo recipients.

Intussusception

In Study 006, 34,837 vaccine recipients and 34,788 placebo recipients were monitored by active surveillance to identify potential cases of intussusception at 7, 14, and 42 days after each dose, and every 6 weeks thereafter for 1 year after the first dose.

For the primary safety outcome, cases of intussusception occurring within 42 days of any dose, there were 6 cases among RotaTeq recipients and 5 cases among placebo recipients (see Table 1). The data did not suggest an increased risk of intussusception relative to placebo.

Table 1: Confirmed cases of intussusception in recipients of RotaTeq as compared with placebo recipients during Study 006
 | RotaTeq (n=34,837) | Placebo (n=34,788)
Confirmed intussusception cases within 42 days of any dose | 6 | 5
Relative risk (95% CI) [Relative risk and 95% confidence interval based upon group sequential design stopping criteria employed in Study 006.] | 1.6 (0.4, 6.4)
Confirmed intussusception cases within 365 days of dose 1 | 13 | 15
Relative risk (95% CI) | 0.9 (0.4, 1.9)

Among vaccine recipients, there were no confirmed cases of intussusception within the 42-day period after the first dose, which was the period of highest risk for the rhesus rotavirus-based product (see Table 2).

Table 2: Intussusception cases by day range in relation to dose in Study 006
 | Dose 1 |  | Dose 2 |  | Dose 3 |  | Any Dose
Day Range | RotaTeq | Placebo | RotaTeq | Placebo | RotaTeq | Placebo | RotaTeq | Placebo
1-7 | 0 | 0 | 1 | 0 | 0 | 0 | 1 | 0
1-14 | 0 | 0 | 1 | 0 | 0 | 1 | 1 | 1
1-21 | 0 | 0 | 3 | 0 | 0 | 1 | 3 | 1
1-42 | 0 | 1 | 4 | 1 | 2 | 3 | 6 | 5

All of the children who developed intussusception recovered without sequelae with the exception of a 9-month-old male who developed intussusception 98 days after dose 3 and died of post-operative sepsis. There was a single case of intussusception among 2,470 recipients of RotaTeq in a 7-month-old male in the phase 1 and 2 studies (716 placebo recipients).

Hematochezia

Hematochezia reported as an adverse experience occurred in 0.6% (39/6,130) of vaccine and 0.6% (34/5,560) of placebo recipients within 42 days of any dose. Hematochezia reported as a serious adverse experience occurred in <0.1% (4/36,150) of vaccine and <0.1% (7/35,536) of placebo recipients within 42 days of any dose.

Seizures

All seizures reported in the phase 3 trials of RotaTeq (by vaccination group and interval after dose) are shown in Table 3.

Table 3: Seizures reported by day range in relation to any dose in the phase 3 trials of RotaTeq
Day range | 1-7 | 1-14 | 1-42
RotaTeq | 10 | 15 | 33
Placebo | 5 | 8 | 24

Seizures reported as serious adverse experiences occurred in <0.1% (27/36,150) of vaccine and <0.1% (18/35,536) of placebo recipients (not significant). Ten febrile seizures were reported as serious adverse experiences, 5 were observed in vaccine recipients and 5 in placebo recipients.

Kawasaki Disease

In the phase 3 clinical trials, infants were followed for up to 42 days of vaccine dose. Kawasaki disease was reported in 5 of 36,150 vaccine recipients and in 1 of 35,536 placebo recipients with unadjusted relative risk 4.9 (95% CI 0.6, 239.1).

Most Common Adverse Events

Solicited Adverse Events

Detailed safety information was collected from 11,711 infants (6,138 recipients of RotaTeq) which included a subset of subjects in Study 006 and all subjects from Studies 007 and 009 (Detailed Safety Cohort). A Vaccination Report Card was used by parents/guardians to record the child's temperature and any episodes of diarrhea and vomiting on a daily basis during the first week following each vaccination. Table 4 summarizes the frequencies of these adverse events and irritability.

Table 4: Solicited adverse experiences within the first week after doses 1, 2, and 3 (Detailed Safety Cohort)
Adverse experience | Dose 1 |  | Dose 2 |  | Dose 3
 | RotaTeq | Placebo | RotaTeq | Placebo | RotaTeq | Placebo
Elevated temperature [Temperature ≥100.5°F [38.1°C] rectal equivalent obtained by adding 1 degree F to otic and oral temperatures and 2 degrees F to axillary temperatures] | n=5,616 17.1% | n=5,077 16.2% | n=5,215 20.0% | n=4,725 19.4% | n=4,865 18.2% | n=4,382 17.6%
 | n=6,130 | n=5,560 | n=5,703 | n=5,173 | n=5,496 | n=4,989
Vomiting | 6.7% | 5.4% | 5.0% | 4.4% | 3.6% | 3.2%
Diarrhea | 10.4% | 9.1% | 8.6% | 6.4% | 6.1% | 5.4%
Irritability | 7.1% | 7.1% | 6.0% | 6.5% | 4.3% | 4.5%

Other Adverse Events

Parents/guardians of the 11,711 infants were also asked to report the presence of other events on the Vaccination Report Card for 42 days after each dose.

Fever was observed at similar rates in vaccine (N=6,138) and placebo (N=5,573) recipients (42.6% vs. 42.8%). Adverse events that occurred at a statistically higher incidence (i.e., 2-sided p-value <0.05) within the 42 days of any dose among recipients of RotaTeq as compared with placebo recipients are shown in Table 5.

Table 5: Adverse events that occurred at a statistically higher incidence within 42 days of any dose among recipients of RotaTeq as compared with placebo recipients
Adverse event | RotaTeq N=6,138 | Placebo N=5,573
 | n (%) | n (%)
Diarrhea | 1,479 (24.1%) | 1,186 (21.3%)
Vomiting | 929 (15.2%) | 758 (13.6%)
Otitis media | 887 (14.5%) | 724 (13.0%)
Nasopharyngitis | 422 (6.9%) | 325 (5.8%)
Bronchospasm | 66 (1.1%) | 40 (0.7%)

Safety in Pre-Term Infants

RotaTeq or placebo was administered to 2,070 pre-term infants (25 to 36 weeks gestational age, median 34 weeks) according to their age in weeks since birth in Study 006. All pre-term infants were followed for serious adverse experiences; a subset of 308 infants was monitored for all adverse experiences. There were 4 deaths throughout the study, 2 among vaccine recipients (1 SIDS and 1 motor vehicle accident) and 2 among placebo recipients (1 SIDS and 1 unknown cause). No cases of intussusception were reported. Serious adverse experiences occurred in 5.5% of vaccine and 5.8% of placebo recipients. The most common serious adverse experience was bronchiolitis, which occurred in 1.4% of vaccine and 2.0% of placebo recipients. Parents/guardians were asked to record the child's temperature and any episodes of vomiting and diarrhea daily for the first week following vaccination. The frequencies of these adverse experiences and irritability within the week after dose 1 are summarized in Table 6.

Table 6: Solicited adverse experiences within the first week of doses 1, 2, and 3 among pre-term infants
 | Dose 1 |  | Dose 2 |  | Dose 3
Adverse event | RotaTeq | Placebo | RotaTeq | Placebo | RotaTeq | Placebo
 | N=127 | N=133 | N=124 | N=121 | N=115 | N=108
Elevated temperature [Temperature ≥100.5°F [38.1°C] rectal equivalent obtained by adding 1 degree F to otic and oral temperatures and 2 degrees F to axillary temperatures] | 18.1% | 17.3% | 25.0% | 28.1% | 14.8% | 20.4%
 | N=154 | N=154 | N=137 | N=137 | N=135 | N=129
Vomiting | 5.8% | 7.8% | 2.9% | 2.2% | 4.4% | 4.7%
Diarrhea | 6.5% | 5.8% | 7.3% | 7.3% | 3.7% | 3.9%
Irritability | 3.9% | 5.2% | 2.9% | 4.4% | 8.1% | 5.4%

6.2 Post-Marketing Experience

The following adverse events have been identified during post-approval use of RotaTeq from reports to the Vaccine Adverse Event Reporting System (VAERS).

Reporting of adverse events following immunization to VAERS is voluntary, and the number of doses of vaccine administered is not known; therefore, it is not always possible to reliably estimate the adverse event frequency or establish a causal relationship to vaccine exposure using VAERS data.

In post-marketing experience, the following adverse events have been reported following the use of RotaTeq:

Immune system disorders:

Anaphylactic reaction

Gastrointestinal disorders:

Intussusception (including death)

Hematochezia

Gastroenteritis with vaccine viral shedding in infants with Severe Combined Immunodeficiency Disease (SCID)

Skin and subcutaneous tissue disorders:

Urticaria

Angioedema

Infections and infestations:

Kawasaki disease

Transmission of vaccine virus strains from vaccine recipient to non-vaccinated contacts.

Post-Marketing Observational Safety Surveillance Studies

The temporal association between vaccination with RotaTeq and intussusception was evaluated in the Post-licensure Rapid Immunization Safety Monitoring (PRISM) program {2}, an electronic active surveillance program comprised of 3 US health insurance plans.

More than 1.2 million RotaTeq vaccinations (507,000 of which were first doses) administered to infants 5 through 36 weeks of age were evaluated. From 2004 through 2011, potential cases of intussusception in either the inpatient or emergency department setting and vaccine exposures were identified through electronic procedure and diagnosis codes. Medical records were reviewed to confirm intussusception and rotavirus vaccination status.

The risk of intussusception was assessed using self-controlled risk interval and cohort designs, with adjustment for age. Risk windows of 1-7 and 1-21 days were evaluated. Cases of intussusception were observed in temporal association within 21 days following the first dose of RotaTeq, with a clustering of cases in the first 7 days. Based on the results, approximately 1 to 1.5 excess cases of intussusception occur per 100,000 vaccinated US infants within 21 days following the first dose of RotaTeq. In the first year of life, the background rate of intussusception hospitalizations in the US has been estimated to be approximately 34 per 100,000 infants.{3}

In an earlier prospective post-marketing observational cohort study conducted using a large US medical claims database, the risks of intussusception or Kawasaki disease resulting in emergency department visits or hospitalizations during the 30 days following any dose of vaccine were analyzed among 85,150 infants receiving one or more doses of RotaTeq from February 2006 through March 2009. Medical charts were reviewed to confirm these diagnoses. Evaluation included concurrent (n = 62,617) and historical (n=100,000 from 2001-2005) control groups of infants who received diphtheria, tetanus and acellular pertussis vaccine (DTaP) but not RotaTeq.

Confirmed intussusception cases in the RotaTeq group were compared with those in the concurrent DTaP control group and in the historical control group. The data were analyzed post-dose 1 and post any dose, in both 7 day and 30 day risk windows. A statistically significant increased risk of intussusception after RotaTeq vaccination was not observed.

One confirmed case of Kawasaki disease (23 days post-dose 3) was identified among infants vaccinated with RotaTeq and one confirmed case of Kawasaki disease (22 days post-dose 2) was identified among concurrent DTaP controls (relative risk = 0.7; 95% CI: 0.01-55.56).

In addition, general safety was monitored by electronic search of the automated records database for all emergency department visits and hospitalizations in the 30-day period after each dose of RotaTeq compared with: 1) days 31-60 after each dose of RotaTeq (self-matched controls) and 2) the 30-day period after each dose of DTaP vaccine (historical control subset from 2004-2005, n=40,000). In safety analyses which evaluated multiple follow-up windows after vaccination (days: 0-7, 1-7, 8-14 and 0-30), no safety concerns were identified for infants vaccinated with RotaTeq when compared with self-matched controls and the historical control subset.

Reporting Adverse Events

Parents or guardians should be instructed to report any adverse reactions to their health care provider.

Health care providers should report all adverse events to the U.S. Department of Health and Human Services' Vaccine Adverse Events Reporting System (VAERS).

VAERS accepts all reports of suspected adverse events after the administration of any vaccine, including but not limited to the reporting of events required by the National Childhood Vaccine Injury Act of 1986. For information or a copy of the vaccine reporting form, call the VAERS toll-free number at 1-800-822-7967 or report online to www.vaers.hhs.gov .{4}

7 DRUG INTERACTIONS

Immunosuppressive therapies including irradiation, antimetabolites, alkylating agents, cytotoxic drugs and corticosteroids (used in greater than physiologic doses), may reduce the immune response to vaccines.

7.1 Concomitant Vaccine Administration

In clinical trials, RotaTeq was administered concomitantly with diphtheria and tetanus toxoids and acellular pertussis (DTaP), inactivated poliovirus vaccine (IPV), H. influenzae type b conjugate (Hib), hepatitis B vaccine, and pneumococcal conjugate vaccine [see Clinical Studies (14)]. The safety data available are in the ADVERSE REACTIONS section [see Adverse Reactions (6.1)]. There was no evidence for reduced antibody responses to the vaccines that were concomitantly administered with RotaTeq.

8 USE IN SPECIFIC POPULATIONS

8.1 Pregnancy

RotaTeq is not approved for individuals 32 weeks of age and older. No human or animal data are available to assess vaccine-associated risks in pregnancy.

8.2 Lactation

No human or animal data are available to assess the impact of RotaTeq on milk production, its presence in breast milk, or its effect on the breastfed infant.

8.4 Pediatric Use

Safety and effectiveness of RotaTeq have not been established in infants less than 6 weeks of age or greater than 32 weeks of age.

Data are available from clinical studies to support the use of RotaTeq in pre-term infants according to their age in weeks since birth [see Adverse Reactions (6.1)].

Data are available from clinical studies to support the use of RotaTeq in infants with controlled gastroesophageal reflux disease.

10 OVERDOSAGE

There have been post-marketing reports of infants who received more than one dose or a replacement dose of RotaTeq after regurgitation [see Dosage and Administration (2.2)]. In limited post-marketing experience of reported overdosage, the adverse events reported after incorrect administration of higher than recommended doses of RotaTeq were similar to adverse events observed with the approved dosage and schedule.

11 DESCRIPTION

RotaTeq is a live, oral pentavalent vaccine that contains 5 live reassortant rotaviruses. The rotavirus parent strains of the reassortants were isolated from human and bovine hosts. Four reassortant rotaviruses express one of the outer capsid proteins (G1, G2, G3, or G4) from the human rotavirus parent strain and the attachment protein (type P7) from the bovine rotavirus parent strain. The fifth reassortant virus expresses the attachment protein, P1A (genotype P[8]), herein referred to as type P1A[8], from the human rotavirus parent strain and the outer capsid protein of type G6 from the bovine rotavirus parent strain (see Table 7).

Table 7
Name of Reassortant | Human Rotavirus Parent Strains and Outer Surface Protein Compositions | Bovine Rotavirus Parent Strain and Outer Surface Protein Composition | Reassortant Outer Surface Protein Composition (Human Rotavirus Component in Bold) | Minimum Dose Levels (10^6 infectious units)
G1 | WI79 – G1P1A[8] | WC3 - G6, P7[5] | G1P7[5] | 2.2
G2 | SC2 – G2P2[6] | WC3 - G6, P7[5] | G2P7[5] | 2.8
G3 | WI78 – G3P1A[8] | WC3 - G6, P7[5] | G3P7[5] | 2.2
G4 | BrB – G4P2[6] | WC3 - G6, P7[5] | G4P7[5] | 2.0
P1A[8] | WI79 – G1P1A[8] | WC3 - G6, P7[5] | G6P1A[8] | 2.3

The reassortants are propagated in Vero cells using standard cell culture techniques in the absence of antifungal agents.

The reassortants are suspended in a buffered stabilizer solution. Each vaccine dose contains sucrose, sodium citrate, sodium phosphate monobasic monohydrate, sodium hydroxide, polysorbate 80, cell culture media, and trace amounts of fetal bovine serum. RotaTeq contains no preservatives.

RotaTeq is a pale yellow clear liquid that may have a pink tint.

The plastic dosing tube and cap do not contain latex.

12 CLINICAL PHARMACOLOGY

Rotavirus is a leading cause of severe acute gastroenteritis in infants and young children, with over 95% of these children infected by the time they are 5 years old.{5} The most severe cases occur among infants and young children between 6 months and 24 months of age.{6}

12.1 Mechanism of Action

The exact immunologic mechanism by which RotaTeq protects against rotavirus gastroenteritis is unknown [see Clinical Studies (14.6)]. RotaTeq is a live viral vaccine that replicates in the small intestine and induces immunity.

13 NONCLINICAL TOXICOLOGY

13.1 Carcinogenesis, Mutagenesis, Impairment of Fertility

RotaTeq has not been evaluated for its carcinogenic or mutagenic potential or its potential to impair fertility.

14 CLINICAL STUDIES

Overall, 73,086 infants were randomized in 4 placebo-controlled, phase 3 studies conducted in 12 countries on 4 continents. The data demonstrating the efficacy of RotaTeq in preventing rotavirus gastroenteritis come from 7,744 of these infants from the US (including Navajo and White Mountain Apache Nations), Finland, and Japan who were enrolled in 3 of these studies: Study 006, Study 007, and Study 029. A fourth trial, Study 009, provided clinical evidence supporting the consistency of manufacture and contributed data to the overall safety evaluation.

The racial distribution of the efficacy subset was as follows: White (RotaTeq 61%, placebo 62%); Hispanic-American (RotaTeq 9%, placebo 8%); Black (2% in both groups); Multiracial (4% in both groups); Asian (10% in both groups); Native American (13% in both groups); and Other (<1% in both groups). The gender distribution was 52% male and 48% female in both vaccination groups.

The efficacy evaluations in these studies included: 1) Prevention of any grade of severity of rotavirus gastroenteritis; 2) Prevention of severe rotavirus gastroenteritis, as defined by a clinical scoring system; and 3) Reduction in hospitalizations due to rotavirus gastroenteritis.

The vaccine was given as a three-dose series to healthy infants with the first dose administered between 6 and 12 weeks of age and followed by two additional doses administered at 4- to 10-week intervals. The age of infants receiving the third dose was 32 weeks of age or less. Oral polio vaccine administration was not permitted; however, other childhood vaccines could be concomitantly administered. Breast-feeding was permitted in all studies.

The case definition for rotavirus gastroenteritis used to determine vaccine efficacy required that a subject meet both of the following clinical and laboratory criteria: (1) greater than or equal to 3 watery or looser-than-normal stools within a 24-hour period and/or forceful vomiting; and (2) rotavirus antigen detection by enzyme immunoassay (EIA) in a stool specimen taken within 14 days of onset of symptoms. The severity of rotavirus acute gastroenteritis was determined by a clinical scoring system that took into account the intensity and duration of symptoms of fever, vomiting, diarrhea, and behavioral changes.

The primary efficacy analyses included cases of rotavirus gastroenteritis caused by types G1, G2, G3, G4 (and G types containing P1A8 (in Study 029 only)) that occurred at least 14 days after the third dose through the first rotavirus season post vaccination.

Analyses were also done to evaluate the efficacy of RotaTeq against rotavirus gastroenteritis caused by any of types G1, G2, G3, and G4 (and G types containing P1A8 (in Study 029 only)) at any time following the first dose through the first rotavirus season postvaccination among infants who received at least one vaccination (Intent-to-treat, ITT).

14.1 Rotavirus Efficacy and Safety Trial (Study 006)

Primary efficacy against any grade of severity of rotavirus gastroenteritis caused by naturally occurring types G1, G2, G3, or G4 through the first rotavirus season after vaccination was 74.0% (95% CI: 66.8, 79.9) and the ITT efficacy was 60.0% (95% CI: 51.5, 67.1). Primary efficacy against severe rotavirus gastroenteritis caused by naturally occurring types G1, G2, G3, or G4 through the first rotavirus season after vaccination was 98.0% (95% CI: 88.3, 100.0), and ITT efficacy was 96.4% (95% CI: 86.2, 99.6). See Table 8.

Table 8: Efficacy of RotaTeq against any grade of severity of and severe [Severe gastroenteritis defined by a clinical scoring system based on the intensity and duration of symptoms of fever, vomiting, diarrhea, and behavioral changes] G1-4 rotavirus gastroenteritis through the first rotavirus season postvaccination in Study 006
 | Per Protocol |  | Intent-to-Treat [ITT analysis includes all subjects in the efficacy cohort who received at least one dose of vaccine.]
 | RotaTeq | Placebo | RotaTeq | Placebo
Subjects vaccinated | 2,834 | 2,839 | 2,834 | 2,839
Gastroenteritis cases
Any grade of severity | 82 | 315 | 150 | 371
Severe | 1 | 51 | 2 | 55
Efficacy estimate % and (95% confidence interval)
Any grade of severity | 74.0 (66.8, 79.9) |  | 60.0 (51.5, 67.1)
Severe | 98.0 (88.3, 100.0) |  | 96.4 (86.2, 99.6)

The efficacy of RotaTeq against severe disease was also demonstrated by a reduction in hospitalizations for rotavirus gastroenteritis among all subjects enrolled in Study 006. RotaTeq reduced hospitalizations for rotavirus gastroenteritis caused by types G1, G2, G3, and G4 through the first two years after the third dose by 95.8% (95% CI: 90.5, 98.2). The ITT efficacy in reducing hospitalizations was 94.7% (95% CI: 89.3, 97.3) as shown in Table 9.

Table 9: Efficacy of RotaTeq in reducing G1-4 rotavirus-related hospitalizations in Study 006
 | Per Protocol |  | Intent-to-Treat [ITT analysis includes all subjects who received at least one dose of vaccine.]
 | RotaTeq | Placebo | RotaTeq | Placebo
Subjects vaccinated | 34,035 | 34,003 | 34,035 | 34,003
Number of hospitalizations | 6 | 144 | 10 | 187
Efficacy estimate % and (95% confidence interval) | 95.8 (90.5, 98.2) |  | 94.7 (89.3, 97.3)

14.2 Study 007

Primary efficacy against any grade of severity of rotavirus gastroenteritis caused by naturally occurring types G1, G2, G3, or G4 through the first rotavirus season after vaccination was 72.5% (95% CI: 50.6, 85.6) and the ITT efficacy was 58.4% (95% CI: 33.8, 74.5). Primary efficacy against severe rotavirus gastroenteritis caused by naturally occurring types G1, G2, G3, or G4 through the first rotavirus season after vaccination was 100% (95% CI: 13.0, 100.0) and ITT efficacy against severe rotavirus disease was 100% (95% CI: 30.2, 100.0) as shown in Table 10.

Table 10: Efficacy of RotaTeq against any grade of severity of and severe [Severe gastroenteritis defined by a clinical scoring system based on the intensity and duration of symptoms of fever, vomiting, diarrhea, and behavioral change] G1-4 rotavirus gastroenteritis through the first rotavirus season postvaccination in Study 007
 | Per Protocol |  | Intent-to-Treat [ITT analysis includes all subjects in the efficacy cohort who received at least one dose of vaccine.]
 | RotaTeq | Placebo | RotaTeq | Placebo
Subjects vaccinated | 650 | 660 | 650 | 660
Gastroenteritis cases
Any grade of severity | 15 | 54 | 27 | 64
Severe | 0 | 6 | 0 | 7
Efficacy estimate % and (95% confidence interval)
Any grade of severity | 72.5 (50.6, 85.6) |  | 58.4 (33.8, 74.5)
Severe | 100.0 (13.0, 100.0) |  | 100.0 (30.2, 100.0)

14.3 Multiple Rotavirus Seasons

The efficacy of RotaTeq through a second rotavirus season was evaluated in a single study (Study 006). Efficacy against any grade of severity of rotavirus gastroenteritis caused by rotavirus types G1, G2, G3, and G4 through the two rotavirus seasons after vaccination was 71.3% (95% CI: 64.7, 76.9). The efficacy of RotaTeq in preventing cases occurring only during the second rotavirus season postvaccination was 62.6% (95% CI: 44.3, 75.4). The efficacy of RotaTeq beyond the second season postvaccination was not evaluated.

14.4 Rotavirus Gastroenteritis Regardless of Type

The rotavirus types identified in the efficacy subset of Study 006 and Study 007 were G1P1A[8]; G2P1[4]; G3P1A[8]; G4P1A[8]; and G9P1A[8].

In Study 006, the efficacy of RotaTeq against any grade of severity of naturally occurring rotavirus gastroenteritis regardless of type was 71.8% (95% CI: 64.5, 77.8) and efficacy against severe rotavirus disease was 98.0% (95% CI: 88.3, 99.9). The ITT efficacy starting at dose 1 was 50.9% (95% CI: 41.6, 58.9) for any grade of severity of rotavirus disease and was 96.4% (95% CI: 86.3, 99.6) for severe rotavirus disease.

In Study 007, the primary efficacy of RotaTeq against any grade of severity of rotavirus gastroenteritis regardless of type was 72.7% (95% CI: 51.9, 85.4) and efficacy against severe rotavirus disease was 100% (95% CI: 12.7, 100). The ITT efficacy starting at dose 1 was 48.0% (95% CI: 21.6, 66.1) for any grade of severity of rotavirus disease and was 100% (95% CI: 30.4, 100.0) for severe rotavirus disease.

14.5 Rotavirus Gastroenteritis by Type

The efficacy against any grade of severity of rotavirus gastroenteritis by type was evaluated in Study 006 and Study 029. The efficacy cohort analysis from Study 006 is shown in Table 11.

Table 11: Type-specific efficacy of RotaTeq against any grade of severity of rotavirus gastroenteritis among infants in Study 006 efficacy cohort through the first rotavirus season postvaccination (Per Protocol)
Type identified by PCR | Number of cases |  | % Efficacy (95% Confidence Interval)
Type identified by PCR | RotaTeq (N=2,834) | Placebo (N=2,839) | % Efficacy (95% Confidence Interval)
G1P1A[8] | 72 | 286 | 74.9 (67.3, 80.9)
G2P1[4] | 6 | 17 | 63.4 (2.6, 88.2)
G3P1A[8] | 1 | 6 | NS
G4P1A[8] | 3 | 6 | NS
G9P1A[8] | 1 | 3 | NS
Unidentified [Includes rotavirus antigen-positive samples in which the specific type could not be identified by PCR] | 11 | 15 | NS
N=number vaccinated
NS=not significant

Additional analyses were conducted to evaluate efficacy in the prevention of rotavirus gastroenteritis due to G9P1A[8].

- In Study 029 (a Phase 3 randomized, blinded, placebo-controlled study conducted in Japan), efficacy on the pre-specified primary endpoint (rotavirus gastroenteritis caused by G1, G2, G3, G4, and G-serotypes associated with serotype P1A[8] (e.g., G9)) was 74.5% (95% CI: 39.9, 90.6). G9P1A[8]-associated gastroenteritis was observed in 0/356 and 5/354 subjects in the RotaTeq and placebo groups, respectively (100% (95% CI: -9.0, 100)).
- In a post hoc analysis of health care utilization data from 68,038 infants (RotaTeq 34,035 and placebo 34,003) in Study 006, using a case definition that included culture confirmation, hospitalization and emergency departments visits for rotavirus gastroenteritis, cases due to G9P1A[8] were reduced (RotaTeq 0 cases: placebo 14 cases) by 100% (95% CI: 69.6, 100.0).

14.6 Immunogenicity

A relationship between antibody responses to RotaTeq and protection against rotavirus gastroenteritis has not been established. In phase 3 studies, 92.9% to 100% of 439 recipients of RotaTeq achieved a 3-fold or more rise in serum anti-rotavirus IgA after a three-dose regimen when compared to 12.3%-20.0% of 397 placebo recipients.

15 REFERENCES

1. Murphy TV, Gargiullo PM, Massoudi MS et al. Intussusception among infants given an oral rotavirus vaccine. N Engl J Med 2001;344:564-572.
2. Yih WK, Lieu TA, Kulldorff M, et al. Intussusception risk after rotavirus vaccination in US infants. Mini-Sentinel. www.mini-sentinel.org.
3. Tate JE, Simonsen L, Viboud C, et al. Trends in intussusception hospitalizations among US infants, 1993-2004: implications for monitoring the safety of the new rotavirus vaccination program. Pediatrics 2008;121(5):e1125-e1132.
4. Centers for Disease Control and Prevention. General recommendations on immunization: recommendations of the Advisory Committee on Immunization Practices (ACIP) and the American Academy of Family Physicians (AAFP). MMWR 2002;51(RR-2):1-35.
5. Parashar UD et al. Global illness and deaths caused by rotavirus disease in children. Emerg Infect Dis 2003;9(5):565-572.
6. Parashar UD, Holman RC, Clarke MJ, Bresee JS, Glass RI. Hospitalizations associated with rotavirus diarrhea in the United States, 1993 through 1995: surveillance based on the new ICD-9-CM rotavirus-specific diagnostic code. J Infect Dis 1998;177:13-7.

16 HOW SUPPLIED/STORAGE AND HANDLING

RotaTeq, 2 mL, a solution for oral use, is a pale yellow clear liquid that may have a pink tint. It is supplied as follows:

NDC 0006-4047-41 package of 10 individually pouched single-dose tubes.

NDC 0006-4047-20 package of 25 individually pouched single-dose tubes.

The plastic dosing tube and cap do not contain latex.

16.1 Storage and Handling

Store and transport refrigerated at 2-8°C (36-46°F). RotaTeq should be administered as soon as possible after being removed from refrigeration. For information regarding stability under conditions other than those recommended, call 1-800-637-2590.

Protect from light.

RotaTeq should be discarded in approved biological waste containers according to local regulations.

The product must be used before the expiration date.

17 PATIENT COUNSELING INFORMATION

Advise the patient to read the FDA-approved patient labeling (Patient Information).

Parents or guardians should be given a copy of the required vaccine information and be given the "Patient Information" appended to this insert. Parents and/or guardians should be encouraged to read the patient information that describes the benefits and risks associated with the vaccine and ask any questions they may have during the visit [see Warnings and Precautions (5) and Patient Information].

Distributed by: Merck Sharp & Dohme LLC
Rahway, NJ 07065, USA

For patent information: www.msd.com/research/patent

Copyright © 2006-2023 Merck & Co., Inc., Rahway, NJ, USA, and its affiliates.
All rights reserved.

uspi-v260-os-2304r026

Patient Information
RotaTeq® (pronounced "RŌ-tuh-tek")
rotavirus vaccine, live, oral, pentavalent

Read this information carefully before your child receives each dose of RotaTeq® in case any information about the vaccine changes. Your child will need 3 doses of the vaccine over the course of a few months. This leaflet is a summary of certain information about RotaTeq and does not take the place of talking with your child's doctor, who can give you more complete information written for health care professionals.

What is RotaTeq?

RotaTeq is an oral vaccine used to help prevent rotavirus infection in children. Rotavirus infection can cause fever, vomiting, and diarrhea that can be severe and can lead to loss of body fluids (dehydration), hospitalization and even death in some children. RotaTeq may not fully protect all children that get the vaccine, and if your child already has the virus it will not help them.

Who should not receive RotaTeq?

Your child should not get RotaTeq if:

- He or she had an allergic reaction after getting a dose of this vaccine.
- He or she is allergic to any of the ingredients of the vaccine. A list of ingredients can be found at the end of this leaflet.
- He or she has Severe Combined Immunodeficiency Disease (SCID).
- He or she has ever had intussusception, a form of blockage of the intestines.

What should I tell the doctor before my child gets RotaTeq?

Tell your doctor if your child:

- Has illness with fever. A mild fever or cold by itself is not reason to delay taking the vaccine.
- Has diarrhea or has been vomiting.
- Has not been gaining weight or is not growing as expected.
- Has a blood disorder.
- Has any type of cancer.
- Has a weak immune system because of a disease (this includes HIV/AIDS).
- Gets treatment or takes medicines that may weaken the immune system (such as high doses of steroids) or has received a blood transfusion or blood products within the past 42 days.
- Was born with gastrointestinal problems, or has had a blockage or abdominal surgery.
- Has regular close contact with a member of family or household who has a weak immune system such as someone with cancer or someone taking medicines that weaken their immune system.

What are the possible side effects of RotaTeq?

The most common side effects reported after taking RotaTeq were diarrhea, vomiting, fever, runny nose and sore throat, wheezing or coughing, and ear infection.

Call your child's doctor or go to the emergency department right away if your child has any of the following problems after getting RotaTeq, even if it has been several weeks since the last dose because these may be signs of a serious problem called intussusception:

- bad vomiting
- bad diarrhea
- severe stomach pain
- blood in the stool.

Intussusception happens when a part of the intestine gets blocked or twisted.

Since FDA approval, reports of infants with intussusception following RotaTeq have been received by the Vaccine Adverse Event Reporting System (VAERS). Intussusception occurred days and sometimes weeks after vaccination. Some infants needed hospitalization, surgery on their intestines, or a special enema to treat this problem. Death due to intussusception has occurred.

A study conducted after approval of RotaTeq showed an increased risk of intussusception in the 21 days after the first dose of RotaTeq, but especially in the first 7 days.

Other reported side effects include:

- allergic reactions, which may be severe and may include face and mouth swelling, difficulty breathing, wheezing, hives, and/or skin rash; and
- Kawasaki disease (a serious condition that can affect the heart; symptoms may include fever, rash, red eyes, red mouth, swollen glands, swollen hands and feet and, if not treated, death can occur).

Call your doctor right away if your child has any side effects that concern you or seem to get worse.

These are NOT all the possible side effects of RotaTeq. You can ask your doctor for a more complete list.

You, as a parent or guardian, may also report any adverse reactions to your child's doctor or directly to VAERS. The VAERS toll-free number is 1-800-822-7967 or report online to www.vaers.hhs.gov .

Events that have been identified or reported as side effects following RotaTeq can happen when no vaccine has been given.

What other important information should I know?

Since FDA approval, the spread of vaccine virus to non-vaccinated contacts has been reported. Tell your doctor if you have someone in your household who has a weak immune system, cancer or is taking medications that can weaken the immune system so that your doctor can provide further advice. Hand washing is recommended after diaper changes to help prevent the spread of vaccine virus.

Can RotaTeq be given with other vaccines?

Your child may get RotaTeq at the same time as other childhood vaccines.

How is RotaTeq given?

The vaccine is given by mouth. Your child will receive 3 doses of the vaccine. The first dose is given when your child is 6 to 12 weeks of age, the second dose is given 4 to 10 weeks later and the third dose is given 4 to 10 weeks after the second dose. The last (third) dose should be given to your child by 32 weeks of age.

Your doctor will gently squeeze the vaccine into your child's mouth (see Figure 1). Your infant may spit out some or all of it. If this happens, the dose does not need to be given again during that visit.

Figure 1

What do I do if my child misses a dose of RotaTeq?

All 3 doses of the vaccine should be given to your child by 32 weeks of age. Your doctor will tell you when your child should come for the follow-up doses. It is important to keep those appointments. If you forget or are not able to go back at the planned time, ask your doctor for advice.

What else should I know about RotaTeq?

This leaflet gives a summary of certain information about the vaccine. If you have any questions or concerns about RotaTeq, talk to your doctor.

What are the ingredients in RotaTeq?

5 live rotavirus strains (G1, G2, G3, G4, and P1).

Sucrose, sodium citrate, sodium phosphate monobasic monohydrate, sodium hydroxide, polysorbate 80 and also fetal bovine serum.

Distributed by: Merck Sharp & Dohme LLC
Rahway, NJ 07065, USA

Copyright © 2008-2023 Merck & Co., Inc., Rahway, NJ, USA, and its affiliates.
All rights reserved.

Revised: 04/2023

usppi-v260-os-2304r022

PACKAGE LABEL

PRINCIPAL DISPLAY PANEL - Carton 10 Single-Dose 2 mL Tubes

NDC 0006-4047-41
10 Single-Dose
2 mL Tubes

Rotavirus Vaccine, Live,
Oral, Pentavalent
RotaTeq®

FOR ORAL USE ONLY. NOT FOR INJECTION.
Administer orally without mixing with any
other vaccines or solutions.

Each 2 mL oral dose contains 5 rotavirus reassortants that have been propagated
in Vero cells. The minimum dose levels (infectious units, IU) are as follows:
G1 (2.2 x 10^6) IU; G2 (2.8 x 10^6) IU; G3 (2.2 x 10^6) IU; G4 (2.0 x 10^6) IU and P1 (2.3 x 10^6) IU.

RotaTeq contains no preservatives.

Rx only